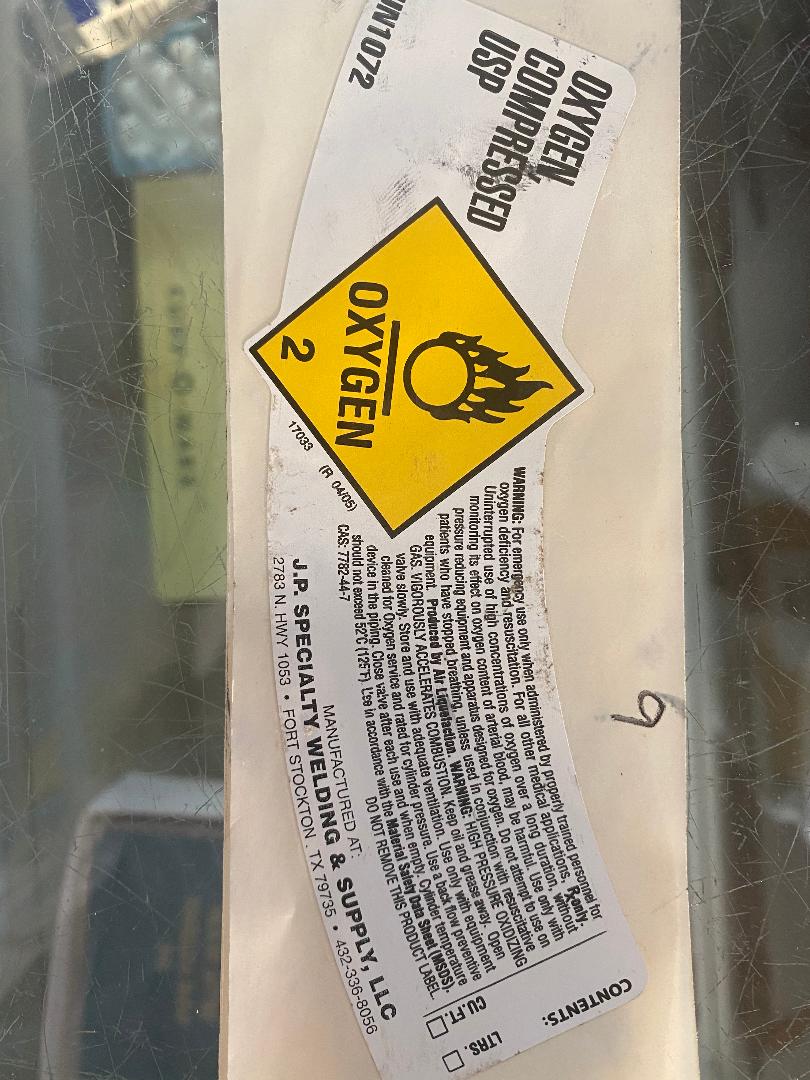 DRUG LABEL: Oxygen
NDC: 81174-560 | Form: GAS
Manufacturer: Jp's Specialty Welding
Category: prescription | Type: HUMAN PRESCRIPTION DRUG LABEL
Date: 20201123

ACTIVE INGREDIENTS: OXYGEN 99 L/100 L

OXYGEN-OXYGEN GAS JP'S SPECIALTY WELDING, LLC

Oxygen

OXYGEN COMPRESSED USP

UN1072

DO NOT REMOVE THIS PRODUCT LABEL

OXYGEN 2

CONTENTS:LTRS. CUFT

WARNING For emergency use only when administered by properly trained personnel for oxygen deficiancy and resuscitation. For all other medical applications, RXonly. Uninterrupted use of high concentrations of oxygen over a long duration, without monitoring its effects on oxygen contentof arterial blood, may be hamful. Use only with pressure reducing equipment and apparatus designed for oxygen. Do not attempt to use on patients who have sopped breathing, unless used in conjunctionwith resusitative equipment. Produced of Air Liquefaction. Warning: HIGH PRESSURE OXIDIZING GAS. VIGEROUSLY ACCELERATED COMBUSTION. Keep oil and grease away. Open valve slowly. Store and use with adequate ventilation. Use only with equipment cleaned for Oxygen service and rated for cylinder pressure. Use a back flow preventative device in the piping.Close valve after each use and when empty. Cylinder temperature should not exceed 52ºC(125ºF). Use in accordance with the Material Safety Data Sheet (MSDS).

DO NOT REMOVE PRODUCT LABEL